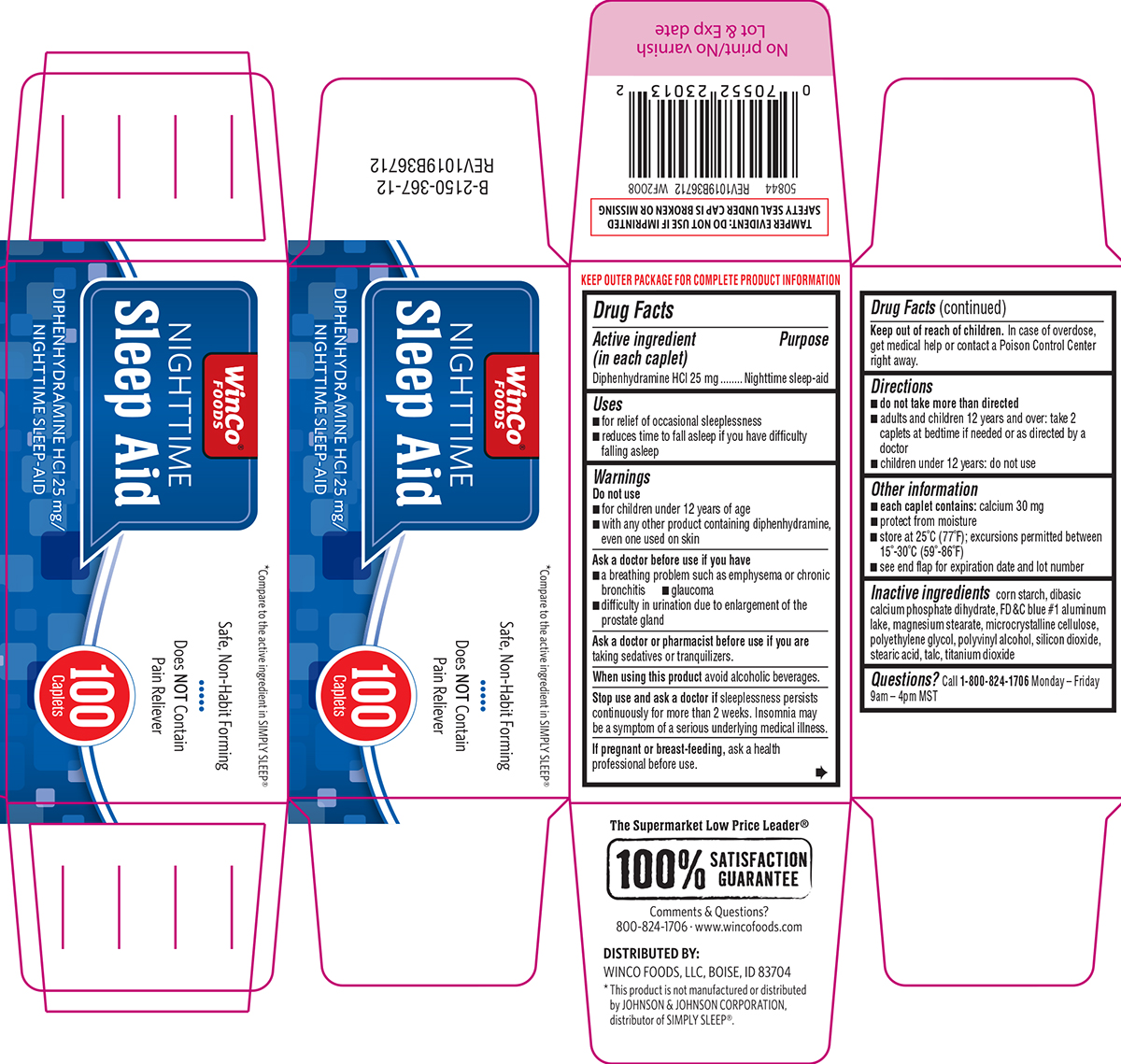 DRUG LABEL: Nighttime Sleep Aid
NDC: 67091-115 | Form: TABLET, FILM COATED
Manufacturer: WinCo Foods, LLC
Category: otc | Type: HUMAN OTC DRUG LABEL
Date: 20260202

ACTIVE INGREDIENTS: DIPHENHYDRAMINE HYDROCHLORIDE 25 mg/1 1
INACTIVE INGREDIENTS: STARCH, CORN; DIBASIC CALCIUM PHOSPHATE DIHYDRATE; FD&C BLUE NO. 1 ALUMINUM LAKE; MAGNESIUM STEARATE; MICROCRYSTALLINE CELLULOSE; POLYETHYLENE GLYCOL, UNSPECIFIED; POLYVINYL ALCOHOL, UNSPECIFIED; SILICON DIOXIDE; STEARIC ACID; TALC; TITANIUM DIOXIDE

Winco 44-367

Active ingredient (in each caplet)

Diphenhydramine HCl 25 mg

Purpose

Nighttime sleep-aid

Uses

- for relief of occasional sleeplessness
- reduces time to fall asleep if you have difficulty falling asleep

Warnings

Do not use

- for children under 12 years of age
- with any other product containing diphenhydramine, even one used on skin

Ask a doctor before use if you have

- a breathing problem such as emphysema or chronic bronchitis
- glaucoma
- difficulty in urination due to enlargement of the prostate gland

Ask a doctor or pharmacist before use if you are

taking sedatives or tranquilizers.

When using this product

avoid alcoholic beverages.

Stop use and ask a doctor if

sleeplessness persists continuously for more than 2 weeks. Insomnia may be a symptom of a serious underlying medical illness.

If pregnant or breast-feeding,

ask a health professional before use.

Keep out of reach of children.

In case of overdose, get medical help or contact a Poison Control Center right away.

Directions

- do not take more than directed
- adults and children 12 years and over: take 2 caplets at bedtime if needed or as directed by a doctor
- children under 12 years: do not use

Other information

- each caplet contains: calcium 30 mg
- protect from moisture
- store at 25ºC (77ºF); excursions permitted between 15º-30ºC (59º-86ºF)
- see end flap for expiration date and lot number

Inactive ingredients

corn starch, dibasic calcium phosphate dihydrate, FD&C blue #1 aluminum lake, magnesium stearate, microcrystalline cellulose, polyethylene glycol, polyvinyl alcohol, silicon dioxide, stearic acid, talc, titanium dioxide

Questions?

Call 1-800-824-1706 Monday - Friday 9am-4pm MST

Principal Display Panel

WinCo®
FOODS

*Compare to the active ingredient in SIMPLY SLEEP®

Safe, Non-Habit Forming

Does NOT Contain
Pain Reliever

NIGHTTIME
Sleep Aid

DIPHENHYDRAMINE HCl 25 mg/
NIGHTTIME SLEEP-AID

100
Caplets

TAMPER EVIDENT: DO NOT USE IF IMPRINTED
SAFETY SEAL UNDER CAP IS BROKEN OR MISSING

The Supermarket Low Price Leader®

100% SATISFACTION
GUARANTEE

Comments & Questions?
800-824-1706 • www.wincofoods.com

DISTRIBUTED BY:
WINCO FOODS, LLC, BOISE, ID 83704

*This product is not manufactured or distributed
by JOHNSON & JOHNSON CORPORATION,
distributor of SIMPLY SLEEP®.

50844 REV1019B36712 WF2008

Winco 44-367